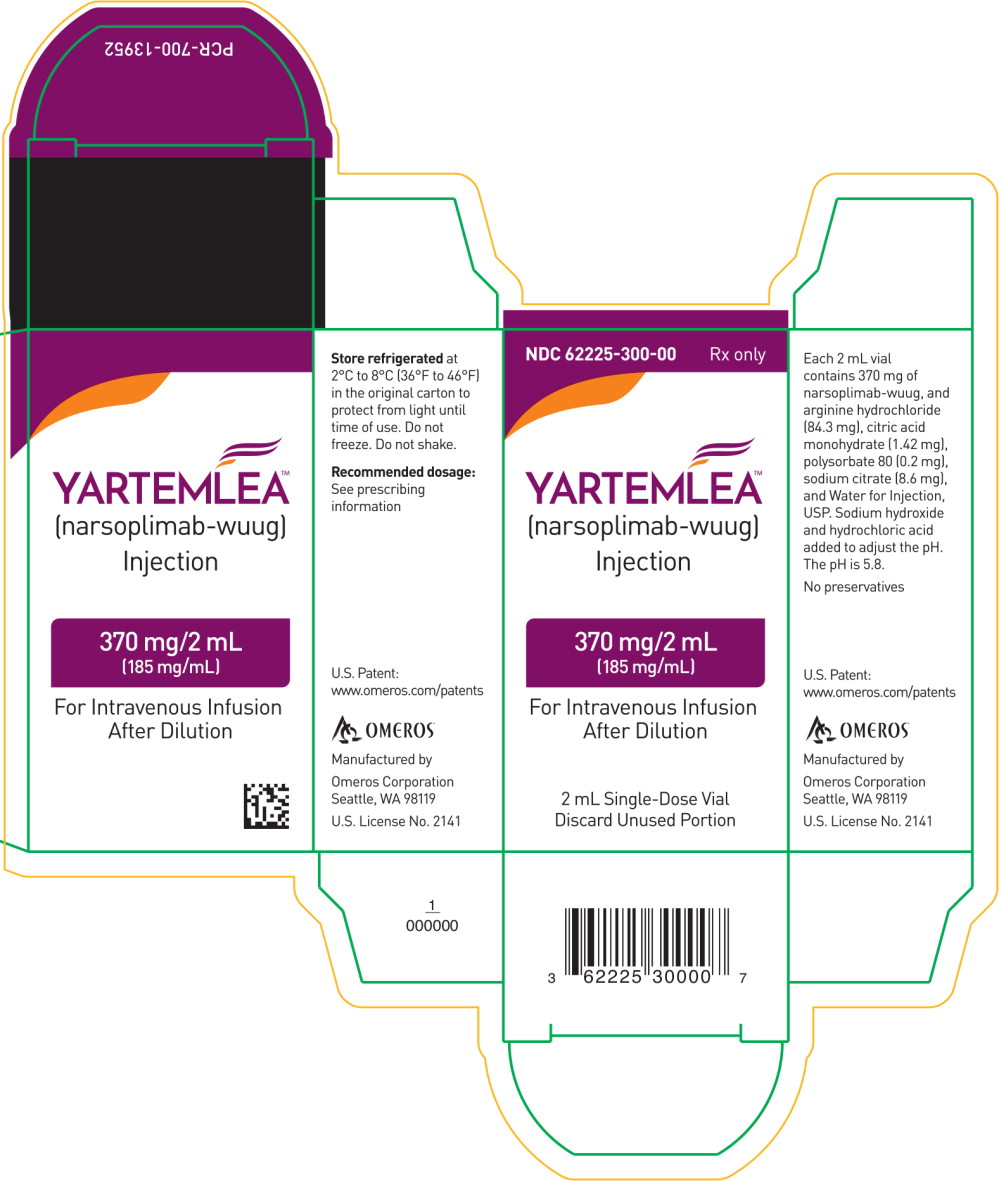 DRUG LABEL: YARTEMLEA
NDC: 62225-300 | Form: INJECTION
Manufacturer: Omeros Corporation
Category: prescription | Type: HUMAN PRESCRIPTION DRUG LABEL
Date: 20260120

ACTIVE INGREDIENTS: NARSOPLIMAB 370 mg/2 mL
INACTIVE INGREDIENTS: ARGININE HYDROCHLORIDE; CITRIC ACID MONOHYDRATE; POLYSORBATE 80; SODIUM CITRATE, UNSPECIFIED FORM; WATER

HIGHLIGHTS OF PRESCRIBING INFORMATION

These highlights do not include all the information needed to use YARTEMLEA safely and effectively. See full prescribing information for YARTEMLEA.
YARTEMLEA (narsoplimab-wuug) injection, for intravenous use
Initial U.S. Approval: 2025

1 INDICATIONS AND USAGE

YARTEMLEA is a MASP-2 inhibitor indicated for the treatment of adult and pediatric patients 2 years of age and older with hematopoietic stem cell transplant-associated thrombotic microangiopathy (TA-TMA). (1)

2 DOSAGE AND ADMINISTRATION

Weight (kg) | Recommended Dosage
Greater than or equal to 50 kg | 370 mg given as an intravenous infusion over 30 minutes once weekly. Increase frequency to twice weekly if there is inadequate improvement in TA-TMA signs and symptoms. (2.1)
Less than 50 kg | 4 mg/kg given as an intravenous infusion over 30 minutes once weekly. Increase frequency to twice weekly if there is inadequate improvement in TA-TMA signs and symptoms. (2.1)

- See Full Prescribing Information for instructions on preparation and administration. (2.2, 2.3, 2.4, 2.5)

3 DOSAGE FORMS AND STRENGTHS

Injection: 370 mg/2 mL (185 mg/mL) in a single-dose vial. (3)

4 CONTRAINDICATIONS

None (4)

5 WARNINGS AND PRECAUTIONS

Serious infections: Monitor patients for signs/symptoms and treat appropriately. (5.1)

6 ADVERSE REACTIONS

Most common adverse reactions (incidence > 20% and independent of causality) are viral infections, sepsis, hemorrhage, diarrhea, vomiting, nausea, neutropenia, pyrexia, fatigue and hypokalemia. (6.1)

To report SUSPECTED ADVERSE REACTIONS, contact Omeros Corporation at 1-844-YARTEM1 or FDA at 1-800-FDA-1088 orwww.fda.gov/medwatch.

FULL PRESCRIBING INFORMATION

1 INDICATIONS AND USAGE

YARTEMLEA is indicated for the treatment of adult and pediatric patients 2 years of age and older with hematopoietic stem cell transplant-associated thrombotic microangiopathy (TA-TMA).

2 DOSAGE AND ADMINISTRATION

2.1 Recommended Dosage

The recommended dosage of YARTEMLEA is provided in Table 1.

Table 1: Recommended Dosage of YARTEMLEA in Adult and Pediatric Patients Two Years of Age and Older with TA-TMA
Weight (kg) | Recommended Dosage
Greater than or equal to 50 kg | 370 mg given as an intravenous infusion over 30 minutes once weekly. Increase frequency to twice weekly if there is inadequate improvement in TA-TMA signs and symptoms.
Less than 50 kg | 4 mg/kg given as an intravenous infusion over 30 minutes once weekly. Increase frequency to twice weekly if there is inadequate improvement in TA-TMA signs and symptoms.

If a dose is missed, administer the dose as soon as possible. Thereafter, resume dosing at the regular scheduled time.

2.2 Important Preparation and Administration Instructions

- Administer diluted YARTEMLEA as an intravenous infusion through a polyvinyl chloride (PVC) or PVC-lined infusion line with a 0.2-micron polyethersulfone (PES) in-line filter and a polyurethane catheter.
- For adults and pediatric patients weighing 10 kg or more, prepare YARTEMLEA in an intravenous bag, diluted to final concentration of 0.8 mg/mL to 8 mg/mLand administer by gravity infusion or via an infusion pump [see Dosage and Administration (2.3and 2.5)] .
- For pediatric patients weighing less than 10 kg, prepare YARTEMLEA in a polypropylene syringe, diluted to final concentration of 0.8 mg/mLand administer via a syringe pump [see Dosage and Administration (2.4and 2.5)] .

2.3 Preparation Instructions into an Intravenous Bag

This section describes preparation of YARTEMLEA for adults and pediatric patients weighing 10 kg or more in an intravenous bag.

1. Preparation

1. Use aseptic technique to prepare YARTEMLEA.
2. Parenteral drug-product vial should be inspected visually for particulate matter and discoloration prior to administration, whenever solution and container permit. YARTEMLEA is a clear to slightly opalescent, slightly yellow to yellow-brown solution. If discoloration or particles are observed in the vial, discard it.
3. Calculate the dose (mg) based on the patient's body weight and the total volume (mL) of YARTEMLEA solution required.
4. Remove the YARTEMLEA vial from the refrigerator and allow the vial to come to room temperature (18°C to 25°C [64°F to 77°F]) for 30 minutes. Vial must be used to prepare the appropriate dosing solution within 4 hours following removal from refrigerated storage.

2. Dilution for Intravenous Bag Infusion

1. Withdraw the required volume of YARTEMLEA solution from the vial using a polypropylene syringe and dilute in a polyvinyl chloride (PVC) infusion bag of 5% Dextrose Injection, USP to make a final concentration of 0.8 mg/mL to 8 mg/mLwith a total volume not to exceed 50 mL.
2. Discard any unused portion left in the vial.
3. Gently invert infusion bag 10 times to mix the diluted solution. Do not shake.
4. Following dilution of YARTEMLEA in the infusion bag, the solution may become opalescent, and small translucent-to-white particles may appear. Discard prepared solution if particulate matter, other than translucent-to-white particles, is observed.

2.4 Preparation Instructions into an Intravenous Syringe

This section describes preparation of YARTEMLEA for pediatric patients weighing less than 10 kg in a syringe.

1. Preparation

1. Use aseptic technique to prepare YARTEMLEA.
2. Parenteral drug-product vial should be inspected visually for particulate matter and discoloration prior to administration, whenever solution and container permit. YARTEMLEA is a clear to slightly opalescent, slightly yellow to yellow-brown solution. If discoloration or particles are observed in the vial, discard it.
3. Calculate the dose (mg) based on the patient's body weight and the total volume (mL) of YARTEMLEA solution required.
4. Remove the YARTEMLEA vial from the refrigerator and allow the vial to come to room temperature (18°C to 25°C [64°F to 77°F]) for 30 minutes. Vial must be used to prepare the appropriate dosing solution within 4 hours following removal from refrigerated storage.

2. Dilution for Intravenous Syringe Infusion

1. Withdraw the required volume of YARTEMLEA solution from the vial using a polypropylene syringe. Discard any unused portion left in the vial.
2. Dilute in 5% Dextrose Injection, USP to make a final concentration of 0.8 mg/mLwith a total volume not to exceed 50 mL.
3. Gently invert syringe 10 times to mix the diluted solution. Do not shake.
4. Following dilution of YARTEMLEA in the syringe, the solution may become opalescent, and small translucent-to-white particles may appear. Discard prepared solution if particulate matter, other than translucent-to-white particles, is observed.
5. Remove air bubbles from the syringe before administration.

2.5 Storage and Administration

Storage of Diluted Product

- If the prepared diluted solution is not used immediately, store the diluted YARTEMLEA solution at room temperature at 18°C to 25°C (64°F to 77°F) for up to 4 additional hours.
- Discard unused YARTEMLEA solution if not used within 4 hours from the time of dilution to the end of the infusion.

Administration

- Administer YARTEMLEA diluted solution intravenously by gravity infusion or via infusion pump (for solution prepared in an intravenous bag) or via syringe pump (for solution prepared in a syringe) over 30 minutes through a PVC or PVC-lined infusion line with a 0.2-micron polyethersulfone (PES) in-line filter and a polyurethane catheter.
- Flush the intravenous line at the end of the infusion with sufficient volume of 5% Dextrose Injection, USP to clear the line of YARTEMLEA infusion solution.
- Do not co-administer other drugs through the same intravenous line.

3 DOSAGE FORMS AND STRENGTHS

Injection: 370 mg/2 mL (185 mg/mL) as a clear to slightly opalescent, slightly yellow to yellow-brown solution in a single-dose vial.

4 CONTRAINDICATIONS

None

5 WARNINGS AND PRECAUTIONS

5.1 Serious Infections

Serious and life-threatening infections have occurred in patients treated with YARTEMLEA.

Serious infections, independent of causality, were reported in 36% (10/28) of patients with TA-TMA receiving YARTEMLEA in clinical trials. These infections included sepsis, viral infections, pneumonia, bacteremia, fungal infection, gastroenteritis, respiratory tract infection and urosepsis.

If YARTEMLEA is administered to patients with active infections, monitor closely for signs and symptoms of worsening infection and treat promptly.

6 ADVERSE REACTIONS

The following clinically significant adverse reactions are described elsewhere in the labeling:

- Serious Infections [see Warnings and Precautions (5.1)]

6.1 Clinical Trial Experience

Because clinical trials are conducted under widely varying conditions, adverse reaction rates observed in the clinical trials of a drug cannot be directly compared to rates in the clinical trials of another drug and may not reflect the rates observed in practice.

The safety data described in this section reflect exposure to YARTEMLEA in the TA-TMA Study in which 28 adult patients received YARTEMLEA. In total, 24 patients received YARTEMLEA at a dose of 4 mg/kg intravenously once weekly for 4 or 8 weeks and 4 patients received 370 mg intravenously weekly for 8 weeks [see Clinical Studies (14)] . The median duration of treatment with YARTEMLEA was 8 weeks (range: 2 to 16.4 weeks).

Serious adverse reactions were reported in 61% of patients receiving YARTEMLEA. Serious adverse reactions in > 5% of patients who received YARTEMLEA included acute kidney injury, confusional state, acute respiratory failure, neutropenic sepsis, septic shock, pulmonary edema, and vomiting. Fatal adverse reactions occurred in 7% of patients, including neutropenic sepsis and septic shock.

Adverse reactions leading to dosage interruptions occurred in 7% of patients who received YARTEMLEA and included Escherichiasepsis, pyrexia, pulmonary alveolar hemorrhage, and acute myocardial infarction.

The most common adverse reactions (≥ 20%) were viral infections, sepsis, hemorrhage, diarrhea, vomiting, nausea, neutropenia, pyrexia, fatigue, and hypokalemia.

Table 2summarizes the adverse reactions, without regard to causality or relatedness to YARTEMLEA, in the TA-TMA Study.

Table 2: Adverse Reactions (≥ 15%) in Patients Receiving YARTEMLEA in the TA-TMA Study
Adverse Reaction | All Grades n (%) N = 28 | Grade ≥ 3 n (%) N = 28
Hemorrhage* | 12 (43) | 2 (7)
Diarrhea | 10 (36) | 2 (7)
Infection, viral* | 10 (36) | 2 (7)
Neutropenia* | 10 (36) | 10 (36)
Pyrexia | 10 (36) | 1 (4)
Vomiting | 9 (32) | 2 (7)
Fatigue* | 8 (29) | 1 (4)
Hypokalemia* | 7 (25) | 3 (11)
Nausea | 7 (25) | 1 (4)
Sepsis* | 7 (25) | 6 (21)
Pneumonia* | 5 (18) | 4 (14)
Hypotension* | 5 (18) | 3 (11)
Abdominal pain* | 5 (18) | 1 (4)
Anemia* | 5 (18) | 3 (11)
Back pain | 5 (18) | 0 (0)
* Grouped terms

An additional 221 adult and pediatric patients with TA-TMA were treated with YARTEMLEA in a global expanded access program (EAP) that included patients for whom YARTEMLEA was their initial treatment following diagnosis of TA-TMA as well as patients who had previously failed or stopped other treatments. The median number of YARTEMLEA doses received by the 221 patients in the EAP was 8 and the median duration of therapy was 5.5 weeks. No new clinically significant safety signals were identified in patients treated in the EAP.

8 USE IN SPECIFIC POPULATIONS

8.1 Pregnancy

Risk Summary

The available data on the use of YARTEMLEA during pregnancy are insufficient to evaluate for a drug-associated risk of major birth defects, miscarriage, or other adverse maternal or fetal outcomes. In animal reproduction studies, narsoplimab-wuug was administered subcutaneously and intravenously twice weekly to pregnant mice and rabbits during organogenesis at dose exposures up to 22 and 91-fold, respectively, the human exposure at the maximum recommended human dose (MRHD) based on area under the concentration-time curve (AUC). There were no adverse effects observed in the absence of maternal toxicity (see Data) .

The background risk of major birth defects and miscarriage for the indicated population is unknown. All pregnancies have a background risk of birth defect, loss, or other adverse outcomes. In the U.S. general population, the estimated background risk of major birth defects and miscarriage in clinically recognized pregnancies is 2 to 4% and 15 to 20%, respectively.

Clinical Considerations

Fetal/Neonatal Adverse Reactions

Transport of endogenous IgG antibodies across the placenta increases as pregnancy progresses and peaks during the third trimester. Therefore, it is expected that YARTEMLEA, following administration, will be present in infants exposed in utero during the third trimester. The potential clinical impact of narsoplimab-wuug exposure on infants exposed in utero should be considered.

Data

Animal Data

Narsoplimab-wuug was administered to pregnant mice at doses of 50, 150, or 300 mg/kg by subcutaneous injection and 300 mg/kg by intravenous injection approximately twice weekly during the major period of organogenesis. Intravenous administration caused reduced body weight gain in dams, reduced fetal body weight up to 4.8%, and an increase of approximately 33% in post-implantation loss at 22-fold the exposure expected at the MRHD (based on AUC) of 4 mg/kg intravenously once weekly in humans. Narsoplimab-wuug was administered to pregnant rabbits at doses of 50 or 150 mg/kg by subcutaneous injection and 150 mg/kg by intravenous injection approximately twice weekly during the major period of organogenesis. Intravenous administration increased post-implantation loss during early gestation days and reduced fetal body weights up to 8.5% below controls at 91-fold the exposure expected at the MRHD (based on AUC) of 4 mg/kg intravenously once weekly in humans.

In an enhanced pre- and postnatal development study, pregnant mice were dosed with narsoplimab-wuug at doses up to 300 mg/kg intravenously twice weekly from day 6 of gestation through lactation. There was a transiently reduced maternal body weight gain but no adverse effects of narsoplimab-wuug on pregnancy nor on the viability, growth, or development of the infants up to 22-fold the exposure expected at the MRHD (based on AUC).

8.2 Lactation

Risk Summary

There are no data on the presence of narsoplimab-wuug in human milk, the effects on the breastfed child, or the effects on milk production. Narsoplimab-wuug is present in the milk of lactating mice (see Data) . When a drug is present in animal milk, it is likely that the drug will be present in human milk. Endogenous maternal IgG and monoclonal antibodies are transferred into human milk. The effects of local gastrointestinal exposure and the extent of systemic exposure in the breastfed child to narsoplimab-wuug are unknown. The developmental and health benefits of breastfeeding should be considered along with the mother's clinical need for YARTEMLEA and any potential adverse effects on the breastfed child from YARTEMLEA or from the underlying maternal condition.

Data

In a pre- and postnatal development study, after subcutaneous and intravenous administration of narsoplimab-wuug to maternal mice, narsoplimab-wuug was detected in the blood of preweaning pups when measured on lactation day 21.

8.4 Pediatric Use

The safety and effectiveness of YARTEMLEA for treatment of TA-TMA have been established in pediatric patients aged 2 years and older. Use of YARTEMLEA for this indication is supported by evidence from studies in adults and in 6 pediatric patients, and additional safety data from 83 more pediatric patients aged 2 years and older [see Adverse Reactions (6.1) and Clinical Studies (14.1)] .

The safety and effectiveness of YARTEMLEA have not been established in pediatric patients younger than 2 years old.

8.5 Geriatric Use

Of the total number of YARTEMLEA-treated patients in the clinical trial and EAP for TA-TMA, 21 (8.4%) were 65 years of age and older, while 1 (0.4%) was at least 75 years of age [see Clinical Studies (14)]. Clinical studies of YARTEMLEA did not include sufficient numbers of subjects at least 65 years of age to determine whether they respond differently than younger subjects. Other reported clinical experience has not identified differences in responses between elderly and younger patients.

10 OVERDOSAGE

There is no known antidote for YARTEMLEA and YARTEMLEA is not dialyzable. If an overdose occurs, institute general supportive measures. Consider contacting the Poison Help line (1-800-222-1222) or a medical toxicologist for additional overdose management recommendations.

11 DESCRIPTION

Narsoplimab-wuug, a mannan-binding lectin-associated serine protease 2 (MASP-2) inhibitor, is a recombinant human immunoglobulin G4 (IgG4) monoclonal antibody produced in Chinese Hamster Ovary cells. The approximate molecular weight is 143 kDa.

YARTEMLEA (narsoplimab-wuug) injection is a sterile, preservative-free, clear to slightly opalescent, slightly yellow to yellow-brown solution for intravenous infusion. Each 2-mL single-dose glass vial contains 370 mg of narsoplimab-wuug, arginine hydrochloride (84.3 mg), citric acid monohydrate (1.42 mg), polysorbate 80 (0.2 mg), sodium citrate (8.6 mg), and Water for Injection, USP. Sodium hydroxide and hydrochloric acid were added to adjust the pH to 5.8.

12 CLINICAL PHARMACOLOGY

12.1 Mechanism of Action

Narsoplimab-wuug inhibits MASP-2, the effector enzyme of the lectin pathway of the complement system, blocking lectin-dependent activation of complement component 3 (C3) and C4 without affecting the classical and alternative pathways of complement.

In hematopoietic stem cell transplant-associated thrombotic microangiopathy (TA-TMA), MASP-2 inhibition is thought to prevent lectin pathway-mediated cellular injury, including endothelial cell injury in small blood vessels.

12.2 Pharmacodynamics

The effect of YARTEMLEA on lectin pathway activity, assessed using inhibition of C4d deposition, was investigated in healthy subjects and patients with TA-TMA (TA-TMA Study). YARTEMLEA concentration levels achieved in patients with TA-TMA resulted in > 80% inhibition of lectin pathway activity. Based on pharmacokinetic/pharmacodynamic (PK/PD) modeling, a wash-out period of 6 weeks is sufficient to reduce YARTEMLEA concentrations to below pharmacologically active levels.

12.3 Pharmacokinetics

The PK profile of narsoplimab-wuug has been characterized in healthy subjects and in patients. PK of narsoplimab-wuug is less than dose-proportional for 2 and 4 mg/kg weekly IV dosing, with an accumulation ratio ranging from 1.02 to 1.75 at 4 mg/kg IV weekly dosing. Narsoplimab-wuug steady state (measured at day 36) geometric mean Cmaxis 36.9 μg/mL, with geometric mean AUC0-tauof 2314 μg·h/mL following 4 mg/kg administered intravenously in healthy subjects. Narsoplimab-wuug steady state is reached after three once-weekly IV doses (day 15) of 4 mg/kg in healthy subjects.

Absorption

After intravenous administration, peak plasma concentrations of narsoplimab-wuug occur approximately at the end of each infusion.

Distribution

Narsoplimab-wuug is distributed in the blood and hydrophilic extravascular space with an average (CV%) volume of distribution of 10.9 L (65%) in patients.

Elimination

Total clearance of narsoplimab-wuug is concentration-dependent, with an estimated mean (CV%) value of 0.12 L/hour (68%) in patients. The mean (CV%) terminal elimination half-life was estimated to be 209 hours (73%) in patients.

Metabolism

Narsoplimab-wuug is expected to be metabolized into small peptides and amino acids by catabolic pathways.

Excretion

No biotransformation or excretion studies have been conducted.

Specific Populations

Body weight was a significant covariate affecting the PK of narsoplimab-wuug. No clinically significant differences in PK of narsoplimab-wuug were observed based on race or sex.

12.6 Immunogenicity

The observed incidence of anti-drug antibodies (ADA) is highly dependent on the sensitivity and the specificity of the assay. Differences in assay methods preclude meaningful comparisons of the incidence of ADA in the narsoplimab-wuug studies described below with the incidence of ADA in other studies.

Anti-Drug Antibody Effects on Pharmacokinetics and Pharmacodynamics

In the 8-week treatment period in the TA-TMA Study, treatment-emergent antibodies to narsoplimab-wuug were detected in 3 of 28 patients (11%) with TA-TMA. One of the 3 patients (33%) developed neutralizing antibodies. There is no apparent correlation of antibody development to PK or PD response, and no alteration in clinical response or adverse events was observed.

13 NONCLINICAL TOXICOLOGY

13.1 Carcinogenesis, Mutagenesis, Impairment of Fertility

Genotoxicity and animal carcinogenicity studies of narsoplimab-wuug have not been conducted.

A fertility study of narsoplimab-wuug in male and female mice produced no adverse effects on reproductive parameters, although a transient decrease in mean body-weight gain in females (premating) and a slight increase in mean percentage of sperm with abnormal morphology in males were observed in the highest dose groups. These effects were noted at exposures corresponding to 21-fold the exposure expected at the MRHD (based on AUC). In the absence of any functional effects on mating, fertility, or reproductive organ weight, these effects on sperm morphology were not considered adverse.

14 CLINICAL STUDIES

The efficacy of YARTEMLEA was assessed in (i) a single-arm, open-label study (TA-TMA Study) that enrolled 28 adult patients who developed TA-TMA following hematopoietic stem-cell transplantation (HCT) and (ii) 19 adult and pediatric patients with TA-TMA with evaluable patient-level response data enrolled in an expanded access program (EAP). In the TA-TMA Study, 24 patients received YARTEMLEA 4 mg/kg intravenously once weekly and 4 patients received YARTEMLEA 370 mg intravenously once weekly. The median number of YARTEMLEA administrations received by the 28 TA-TMA Study patients plus the 19 EAP patients was 8 (range: 2-34), and the median duration of therapy was 8 weeks (range: 2-16 weeks).

Baseline demographic and disease-related characteristics are shown in Table 3. The TA-TMA Study patients had a confirmed diagnosis of TA-TMA per the diagnostic criteria as follows: platelet count < 150,000/μL, evidence of microangiopathic hemolysis (presence of schistocytes, serum LDH greater than the upper limit of normal [ULN] and/or haptoglobin less than the lower limit of normal [LLN]), and renal dysfunction. Patients in the EAP were similarly thrombocytopenic with evidence of microangiopathic hemolytic anemia.

Table 3: Characteristics of TA-TMA Patients Treated with YARTEMLEA in the TA-TMA Study and Expanded Access Program
Parameter | TA-TMA Study | Expanded Access Program (N = 19) a
Parameter | Adult (N = 28) | Pediatric (n = 6) | Adult (n = 13)
Median age (years) (range) | 48 (22, 68) | 10.5 (5, 15) | 62 (19, 71)
Race, n (%)b White Asian Black or African American Native Hawaiian or Other Pacific Islander Other | 17 (61) 7 (25) 2 (7) 1 (4) 1 (4) | -- | --
Ethnicity, n (%)a Hispanic or Latino/a Not Hispanic or Latino/a | 2 (7) 26 (93) | -- | --
Gender, n (%) Male Female | 20 (71) 8 (29) | 2 (33) 4 (67) | 5 (38) 8 (62)
Elevated LDH ≥ 2x ULN, n (%) | 20 (71) | 6 (100) | 7 (54)
Grade II-IV acute GvHD, n (%) | 19 (68) | 5 (83) | 11 (85)
Organ dysfunction, n (%) | 27 (96) | 6 (100) | 13 (100)
Renal dysfunction, n (%) | 21 (75) | 5 (83) | 13 (100)
Pulmonary dysfunction, n (%) | 5 (18) | 0 (0) | 2 (15)
Neurological dysfunction, n (%) | 16 (57) | 2 (33) | 4 (31)
Infection, n (%) | 24 (86) | 6 (100) | 8 (62)
aIncludes patients from EAP with available patient-level data. The entire EAP consisted of 221 patients; patient-level response data were available in 13 adult and 6 pediatric patients.
bRace and ethnicity data were not available for the 19 patients in the EAP.

Among patients in the TA-TMA Study, the median time from HCT to TMA diagnosis was 73.5 days (range: 21–436) and the median time from TMA diagnosis to first dose of narsoplimab was 13.5 days (range: 4–196). Among the 19 adult and pediatric patients in the EAP, the median time from HCT to TMA diagnosis was 81 days (range: 24–452) and the median time from TMA diagnosis to first dose of narsoplimab was 3 days (range: 0–52).

The primary efficacy assessment of YARTEMLEA was based on TMA response defined as improvement in both of two laboratory TMA markers (LDH and platelet counts) and either improvement in organ function or independence from transfusions. The same response criteria were applied to both the TA-TMA Study and EAP patients.

Improvement in platelet count was defined as follows:

- For baseline platelet count ≤ 20,000/μL: (i) ≥ 3-fold increase in platelet count, (ii) post-baseline platelet count ≥ 30,000/μL, and (iii) receipt of no platelet transfusions within 2 days prior to the platelet count assessment.
- For baseline platelet count > 20,000/μL: (i) ≥ 50% increase in platelet count, (ii) platelet count ≥ 75,000/μL, and (iii) receipt of no platelet transfusions within 2 days prior to the platelet count assessment.

To meet LDH improvement criteria, LDH levels were required to be < 1.5x ULN.

In the TA-TMA Study and the EAP, TA-TMA response was achieved in 17/28 (60.7%) and 13/19 (68.4%) patients, respectively (Table 4).

Table 4: Efficacy Results for TA-TMA Study and Expanded Access Program
 | TA-TMA Study | Expanded Access Program (N = 19)
 | Adult (N = 28) | Pediatric (n = 6) | Adult (n = 13)
TMA response 95% CIa | 17/28 (61%) (40.6, 78.5) | 4/6 (67%) (22.3, 95.7) | 9/13 (69%) (38.6, 90.9)
Improvement in TMA markers Platelet count LDH | 17/28 (61%) 14/23 (61%)b 21/28 (75%) | 4/6 (67%) 4/6 (67%) 5/6 (83%) | 9/13 (69%) 9/13 (69%) 11/13 (85%)
Improvement in organ function | 20/27 (74%)b | 5/6 (83%) | 11/13 (85%)
Freedom from red blood cell or platelet transfusionc | 12/25 (48%)b | 3/5 (60%)b | 9/13 (69%)
aConfidence intervals were calculated using the exact (Clopper–Pearson) method.
bThese component findings are based on the number of patients with evaluable data.
cDefined as no transfusions for at least 4 weeks from the last transfusion; only evaluated in patients who received transfusions within the 2 weeks prior to or on the first narsoplimab dose date.

In the TA-TMA Study, the 100-day survival from time of TMA diagnosis was 73.4% (95% CI: 52.2, 86.4). In the EAP cohort (N = 19), 100-day survival from time of TMA diagnosis was 73.7% (95% CI: 47.9, 88.1)

16 HOW SUPPLIED/STORAGE AND HANDLING

YARTEMLEA (narsoplimab-wuug) injection is a sterile, preservative-free, clear to slightly opalescent, slightly yellow to yellow-brown solution supplied as one 370 mg/2 mL (185 mg/mL) single-dose vial in a carton (NDC 62225-300-00).

Store YARTEMLEA vials refrigerated at 2°C to 8°C (36°F to 46°F) in the original carton to protect from light until time of use. Do not freeze. Do not shake. Do not use beyond the expiration date stamped on the carton.

17 PATIENT COUNSELING INFORMATION

Serious infections: Inform patients and caregivers that treatment with complement inhibitors has been associated with an increased risk of serious infections. As YARTEMLEA is a complement inhibitor, advise patients and/or caregivers to immediately report any signs or symptoms suggestive of infections [see Warnings and Precautions (5.1)] .

Manufactured by:

Omeros Corporation

201 Elliott Avenue West

Seattle, WA 98119

US license 2141

This product, or its use, may be covered by one or more US patents, including US Patent Nos. 9,011,860, 10,047,165, and 10,683,367, in addition to others, including patents pending.

YARTEMLEA is a trademark of Omeros Corporation.

© 2025 Omeros Corporation

Principal Display Panel - 370mg Carton Label

NDC 62225-300-00Rx only

YARTEMLEA™

(narsoplimab-wuug)
Injection

370 mg/2 mL
(185 mg/mL)

For Intravenous Infusion After Dilution

2 mL Single-Dose Vial
Discard Unused Portion